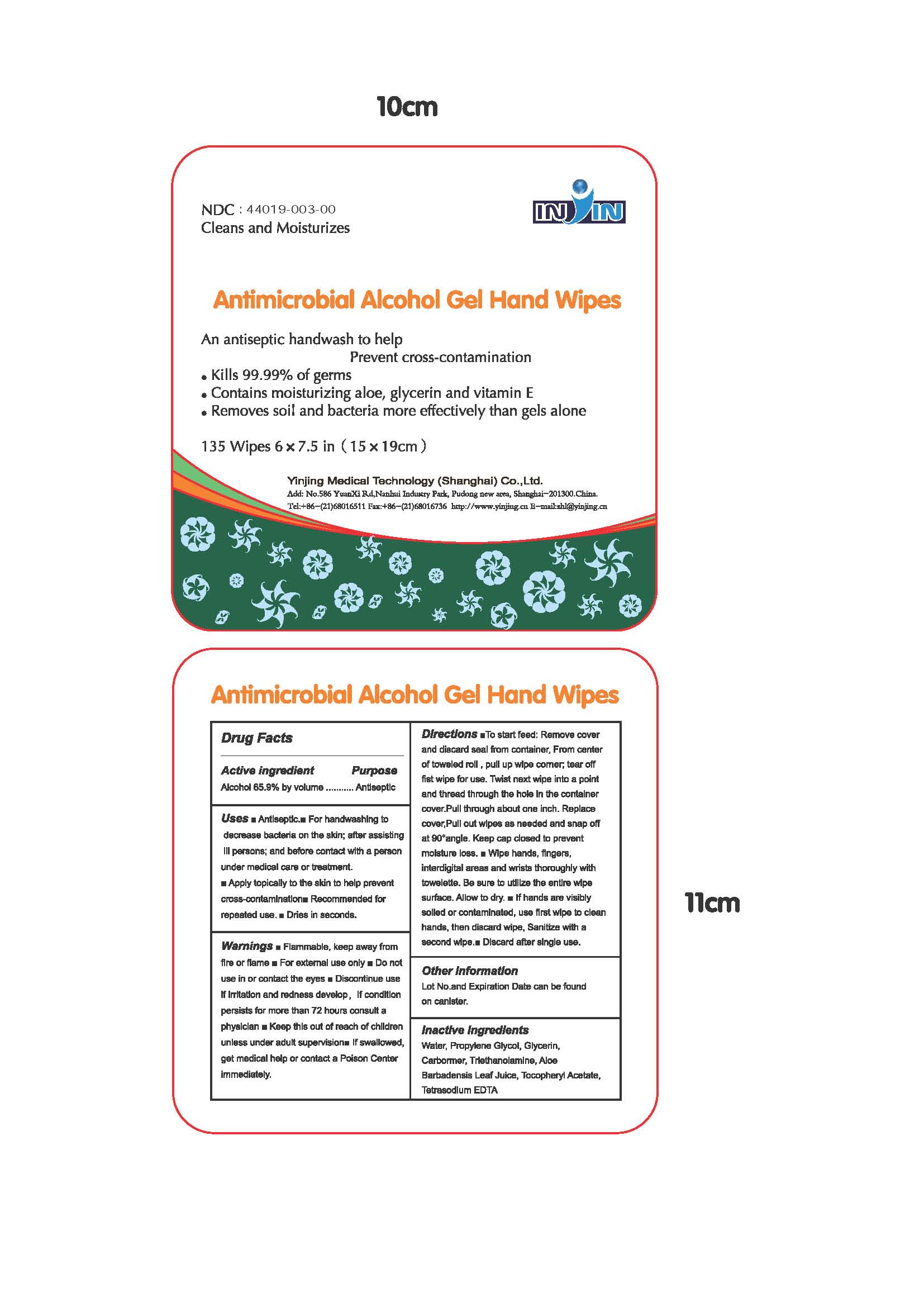 DRUG LABEL: Antimicrobial Alcohol Hand wipes
NDC: 44019-003 | Form: LIQUID
Manufacturer: Yinjing Medical Technology (Shanghai) Co., Ltd.
Category: otc | Type: HUMAN OTC DRUG LABEL
Date: 20171227

ACTIVE INGREDIENTS: ALCOHOL 65.9 g/100 g
INACTIVE INGREDIENTS: WATER; PROPYLENE GLYCOL; GLYCERIN; TROLAMINE; ALOE VERA LEAF; .ALPHA.-TOCOPHEROL ACETATE; EDETATE SODIUM

Antimicrobial Alcohol Gel Hand wipes

Active ingredient

Alcohol 65.9% by volume

Purpose

Antiseptic

Uses

- Antiseptic.
- For hand washing to decrease bacteria on the skin; after assisting ill persons; and before contact with a person under medical care or treatment.
- Apply topically to the skin to help prevent cross-contamination
- Recommended for repeated use.
- Dries in seconds.

Warnings

- Flammable, keep away from fire or flame
- For external use only

• Do not use

in or contact the eyes

• Discontinue use

if irritation and redness develop，If condition persists for more than 72 hours consult a physician

• Keep this out of reach of children

unless under adult supervision • If swallowed, get medical help or contact a Poison Center immediately.

Directions

- To start feed: Remove cover and discard seal from container, From center of toweled roll , pull up wipe corner; tear off fist wipe for use. Twist next wipe into a point and thread through the hole in the container cover.Pull through about one inch. Replace cover,Pull out wipes as needed and snap off at 90°angle. Keep cap closed to prevent moisture loss.
- Wipe hands, fingers, interdigital areas and wrists thoroughly with towelette. Be sure to utilize the entire wipe surface. Allow to dry.
- If hands are visibly soiled or contaminated, use first wipe to clean hands, then discard wipe, Sanitize with a second wipe.
- Discard after single use.

Other information

Lot No.and Expiration Date can be found on canister.

Inactive ingredients

Water, Propylene Glycol, Glycerin, Carbormer, Triethanolamine, Aloe Barbadensis Leaf Juice, Tocopheryl Acetate, Tetrasodium EDTA

Antimicrobial Alcohol Gel Hand Wipes

Shanghai Yinjing Medical Supplies Co.,Ltd.
Add: No.586 YuanXi Rd,Nanhui Industry Park, Pudong new area, Shanghai-201300.China.
Tel:+86-(21)68016511 Fax:+86-(21)68016736 http://www.yinjing.cn E-mail:zhl@yinjing.cn

PACKAGE LABEL

NDC xxxxxxxx-xx
Cleans and Moisturizes IN IN

Antimicrobial Alcohol Gel Hand Wipes
An antiseptic hand wash to help Prevent cross-contamination

- Kills 99.99% of germs
- Contains moisturizing aloe, glycerin and vitamin E
- Removes soil and bacteria more effectively than gels alone